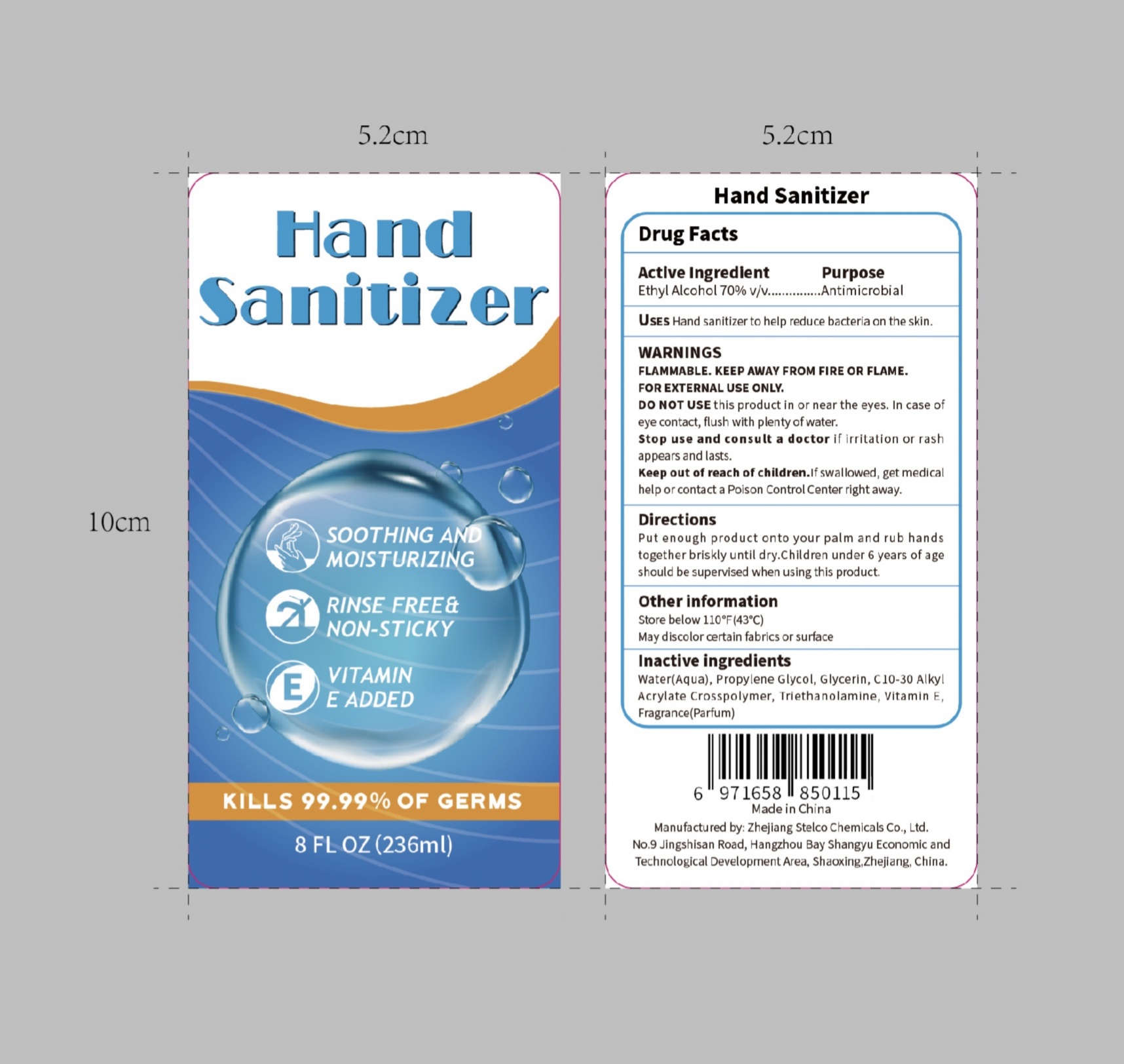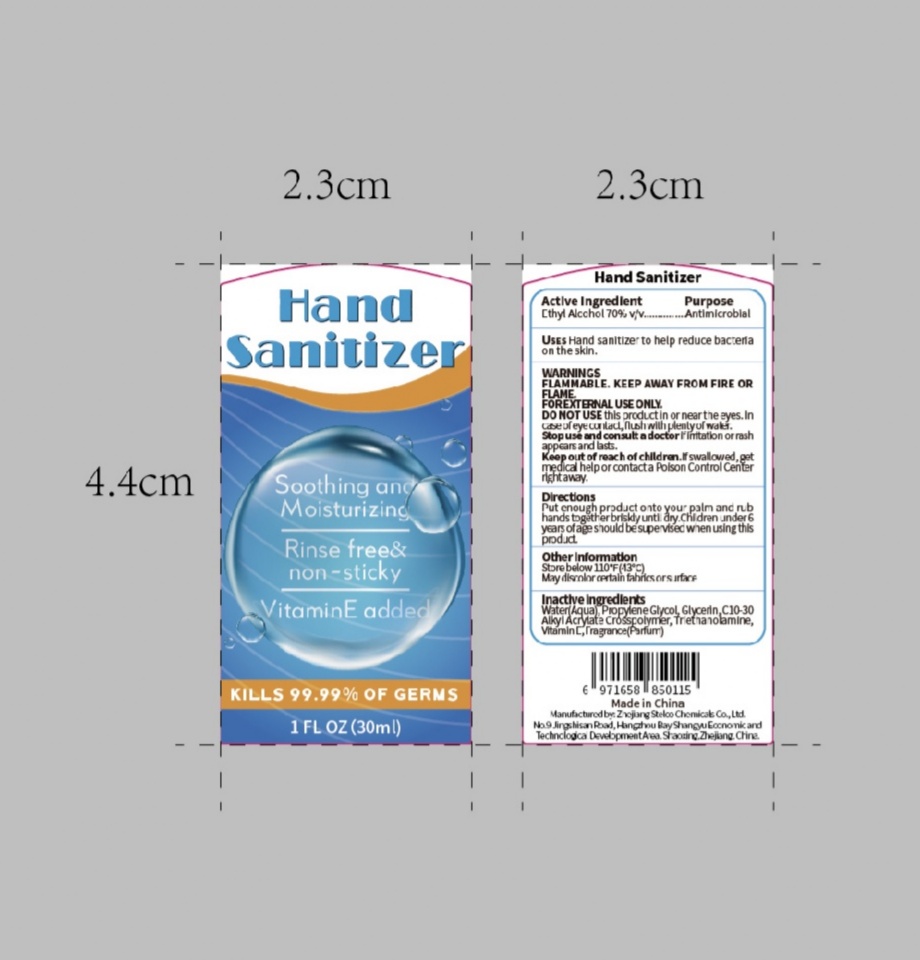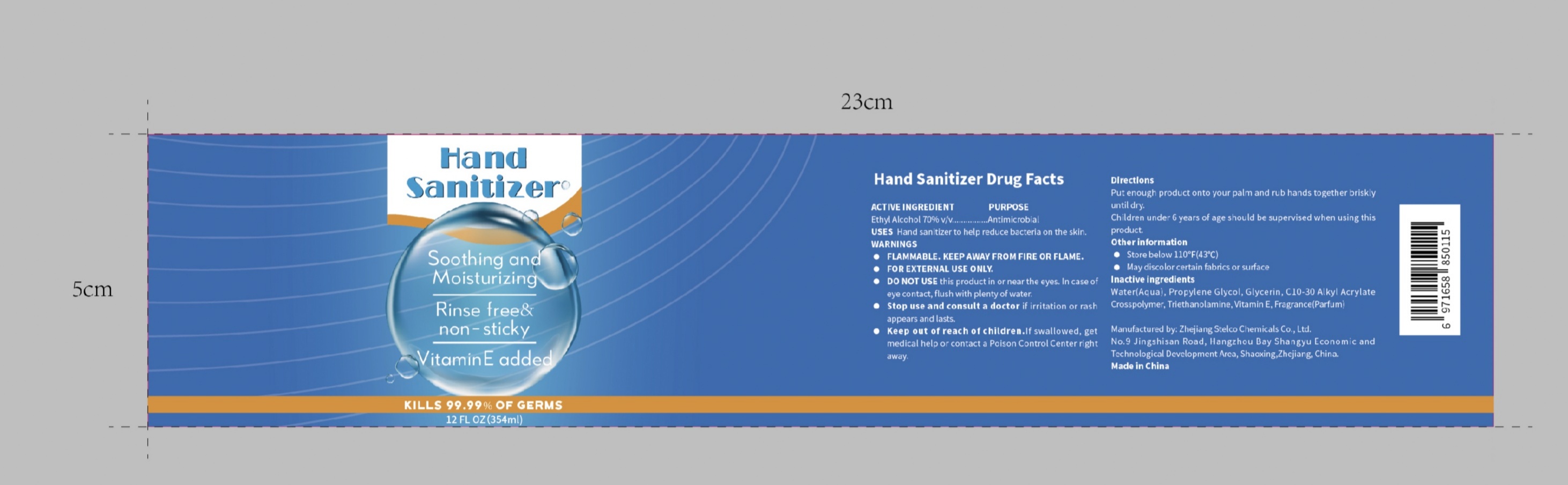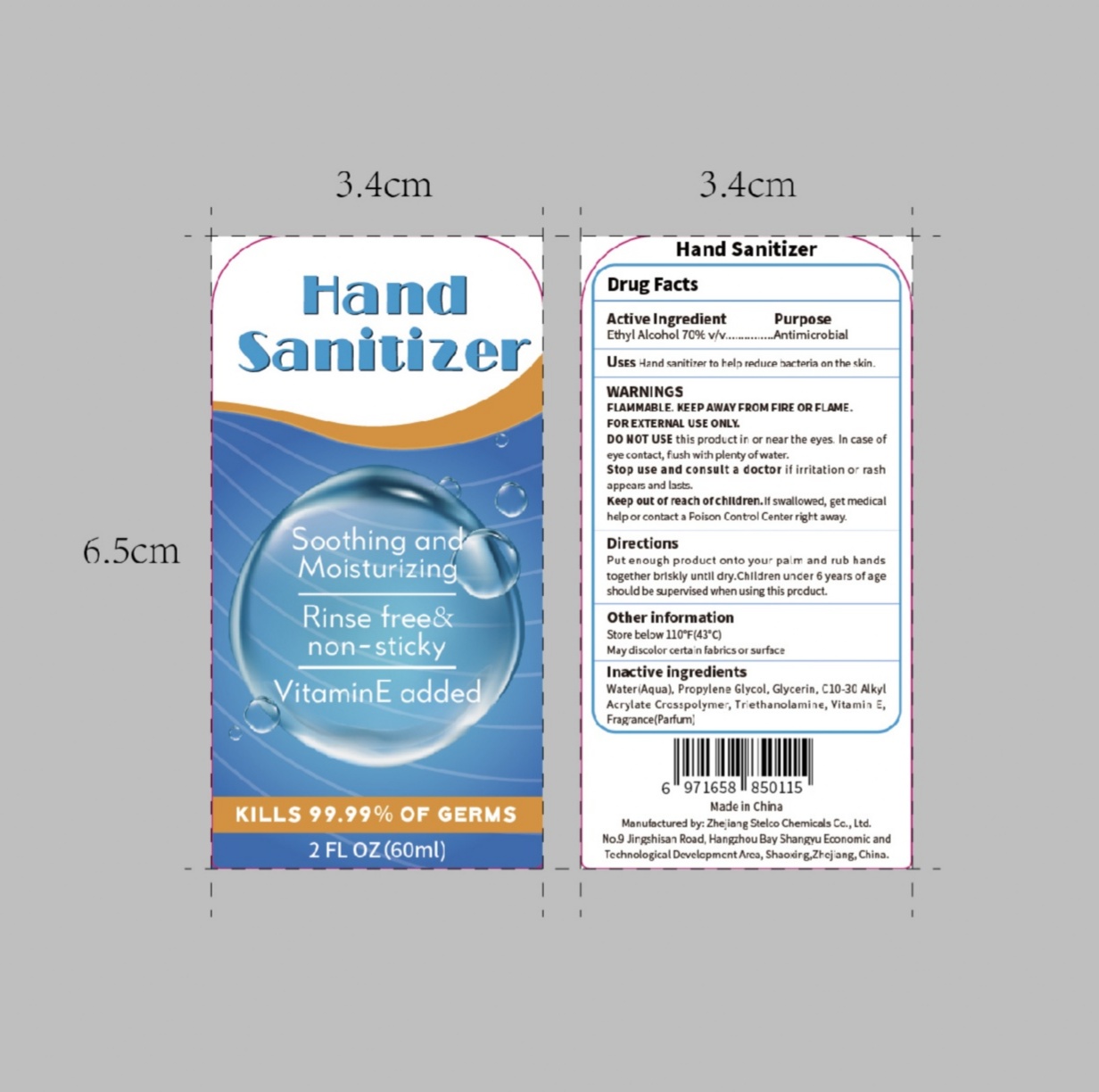 DRUG LABEL: Hand Sanitizer
NDC: 75705-005 | Form: GEL
Manufacturer: ZHEJIANG STELCO CHEMICALS CO. LTD
Category: otc | Type: HUMAN OTC DRUG LABEL
Date: 20200505

ACTIVE INGREDIENTS: ALCOHOL 75 mL/100 mL
INACTIVE INGREDIENTS: PROPYLENE GLYCOL; .ALPHA.-TOCOPHEROL ACETATE; GLYCERIN; TROLAMINE; WATER

Active Ingredient(s)

Ethyl Alcohol 70% v/v....Antimicrobial

Purpose

Antimicrobial, Hand Sanitizer

Use

Hand sanitizer to help reduce bacteria on the skin

Warnings

WARNING SFLAMMABLE. KEEP AWAY FROM FIRE OR FLAMEFOR EXTERNAL USE ONLY

DO NOT USE this product in or near the eyes. In case ofeye contact, flush with plenty of water.

WHEN USING

/

Stop use and consult a doctor if irritation or rash appears and lasts

Keep out of reach of children. If swallowed, get medical help or contact a Poison Control Center right away.

Directions

Put enough product onto your palm and rub handstogether briskly until dry. Children under 6 years of ages hould be supervised when using this product.

Other information

- Store between 15-30C (59-86F)
- Avoid freezing and excessive heat above 40C (104F)

Inactive ingredients

Water(Aqua), Propylene Glycol, Glycerin, C10-30 AlkylAcrylate Crosspolymer, Triethanolamine, Vitamin E, Fragrance(Parfum)